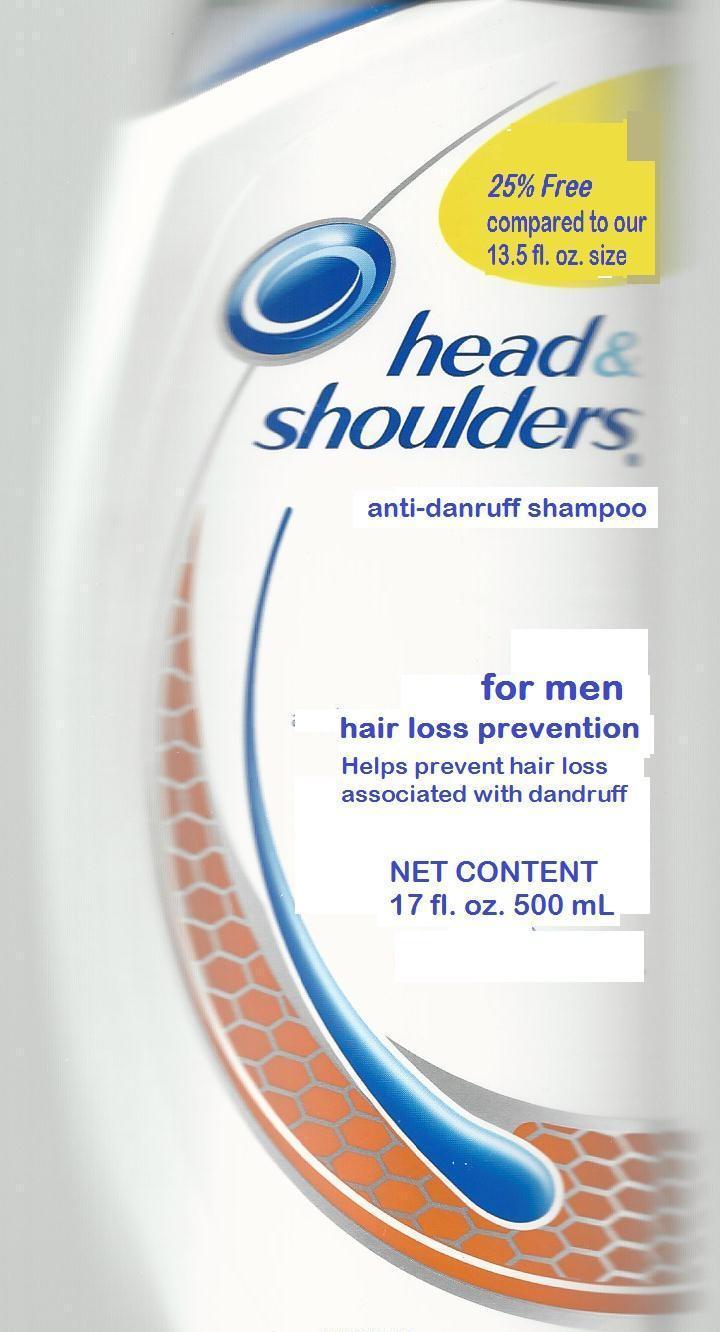 DRUG LABEL: Head and Shoulders
NDC: 51769-140 | Form: SHAMPOO
Manufacturer: ALL NATURAL DYNAMICS
Category: otc | Type: HUMAN OTC DRUG LABEL
Date: 20130201

ACTIVE INGREDIENTS: Pyrithione Zinc 0.01 g/1 mL
INACTIVE INGREDIENTS: Water; Sodium laureth sulfate; Sodium lauryl sulfate; Coco Monoethanolamide; Zinc carbonate; Glycol distearate; Dimethicone; Guar hydroxypropyltrimonium chloride (1.7 substituents per saccharide); Magnesium sulfate; Sodium benzoate; magnesium carbonate hydroxide; Benzyl alcohol; .ALPHA.-TOCOPHEROL ACETATE; FD&C Yellow No. 5; methylchloroisothiazolinone; methylisothiazolinone; FD&C Blue no. 1

Head and Shoulders hair loss prevention

Drug Facts

Active ingredient

Pyrithione zinc 1%

Purpose

Anti-dandruff

Uses

helps prevent recurrence of flaking and itching associated with dandruff.

helps prevent hair loss

Warnings

For external use only.

When using this product

- avoid contact with eyes. If contact occurs, rinse eyes thoroughly with water.

Stop use and ask a doctor if

- condition worsens or does not improve after regular use of this product as directed.

KEEP OUT OF REACH OF CHILDREN

Keep this and all drugs out of reach of children. If swallowed, get medical help or contact a Poison Control Center right away.

Directions

- for maximum dandruff control, use every time you shampoo.
- wet hair, massage onto scalp, rinse, repeat if desired.
- for best results use at least twice a week or as directed by a doctor.

Inactive ingredients

Water, Sodium laureth sulfate, Sodium lauryl sulfate, Coco Monoethanolamide, Zinc carbonate, Glycol distearate, Dimethicone, Guar hydroxypropyltrimonium chloride, Magnesium sulfate, Sodium benzoate, Magnesium carbonate hydroxide, Benzyl alcohol, Tocopheryl acetate, FD&C Yellow No. 5, Methylchloroisothiazolinone, Methylisothiazolinone, FD&C Blue no. 1

Questions (or comments)?

01-800-717-2413

Dist. by

Procter & Gamble Manufactura, S. de R.L. de C.V.

San Andr`s Atoto No. 326, Naucalpan de Juarez,

Estado de Mexico, MX

www.headandshoulders.com